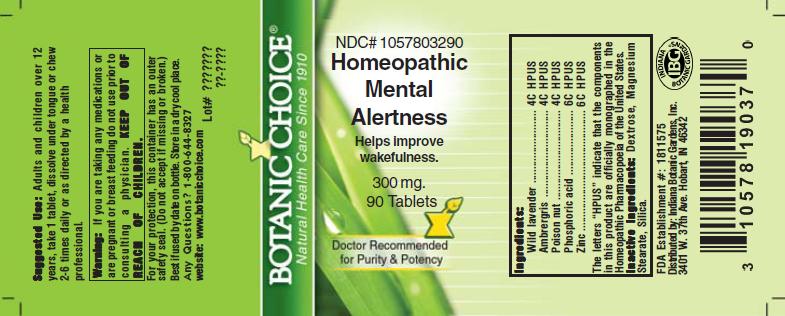 DRUG LABEL: Homeopathic Mental Alertness Formula
NDC: 10578-032 | Form: TABLET
Manufacturer: Indiana Botanic Gardens
Category: homeopathic | Type: HUMAN OTC DRUG LABEL
Date: 20110325

ACTIVE INGREDIENTS: CHASTE TREE 4 [hp_C]/1 1; AMBERGRIS 4 [hp_C]/1 1; STRYCHNOS NUX-VOMICA SEED 4 [hp_C]/1 1; PHOSPHORIC ACID 6 [hp_C]/1 1; ZINC 6 [hp_C]/1 1
INACTIVE INGREDIENTS: DEXTROSE; MAGNESIUM STEARATE ; SILICON DIOXIDE 

Homeopathic Mental Alertness Formula

ACTIVE INGREDIENT

I n g r e d i e n t s :

Wild lavender............................. 4C HPUS
Ambrergris.............................. 4C HPUS

Poison nut............................... 4C HPUS
Phosphoric acid................ 6C HPUS
Zinc..................... 6C HPUS

The letters “HPUS” indicate that the components in
this product are officially monographed in the
Homeopathic Pharmacopoeia of the United States.

PURPOSE

Helps improve wakefulness

KEEP OUT OF
REACH OF CHILDREN.

INDICATIONS AND USAGE

Helps improve wakefulness

WARNINGS

Warning: If you are taking any medications or
are pregnant or breast feeding do not use prior to
consulting a physician.

DOSAGE AND ADMINISTRATION

Suggested Use: Adults and children over 12
years, take 1 tablet, dissolve under tongue or
chew 2-6 times daily, or as directed by a health care
professional.

Inactive Ingredients: Dextrose, Magnesium
Stearate, Silica.

PACKAGE LABEL

NDC# 1057803290

Homeopathic Mental Alertness Formula

Helps improve wakefulness

300 mg.
90 Tablets

USER SAFETY WARNINGS

For your protection, this container has an outer
safety seal. (Do not accept if missing or broken.)
Best if used by date on bottle. Store in a dry cool place.
Any Questions? 1-800-644-8327
website: www.botanicchoice.com

FDA Establishment #: 1811575

Distributed by: Indiana Botanic Gardens, Inc.
3401 W. 37th Ave. Hobart, IN 46342